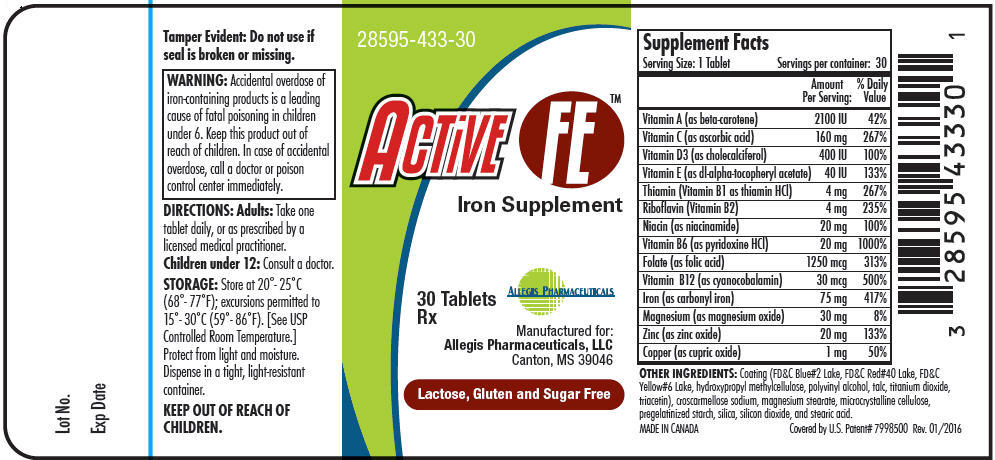 DRUG LABEL: Active FE
NDC: 28595-433 | Form: TABLET
Manufacturer: Allegis Pharmaceuticals, LLC
Category: other | Type: DIETARY SUPPLEMENT
Date: 20160119

ACTIVE INGREDIENTS: .BETA.-CAROTENE 2100 [iU]/1 1; ASCORBIC ACID 160 mg/1 1; CHOLECALCIFEROL 400 [iU]/1 1; .ALPHA.-TOCOPHEROL ACETATE, DL- 40 [iU]/1 1; THIAMINE HYDROCHLORIDE 4 mg/1 1; RIBOFLAVIN 4 mg/1 1; NIACINAMIDE 20 mg/1 1; PYRIDOXINE HYDROCHLORIDE 20 mg/1 1; FOLIC ACID 1250 ug/1 1; CYANOCOBALAMIN 30 ug/1 1; IRON PENTACARBONYL 75 mg/1 1; MAGNESIUM OXIDE 30 mg/1 1; ZINC OXIDE 20 mg/1 1; CUPRIC OXIDE 1 mg/1 1
INACTIVE INGREDIENTS: FD&C YELLOW NO. 6; FD&C BLUE NO. 2; FD&C RED NO. 40; HYPROMELLOSES; POLYVINYL ALCOHOL; TRIACETIN; TALC; TITANIUM DIOXIDE; CROSCARMELLOSE SODIUM; MAGNESIUM STEARATE; CELLULOSE, MICROCRYSTALLINE; STARCH, CORN; SILICON DIOXIDE; STEARIC ACID

Active FE™

HEALTH CLAIM

Iron Supplement
Rx

STATEMENT OF IDENTITY

Supplement Facts
Serving Size: 1 Tablet | Servings per container: 30
 | Amount Per Serving: | % Daily Value
Vitamin A (as beta-carotene) | 2100 IU | 42%
Vitamin C (as ascorbic acid) | 160 mg | 267%
Vitamin D3 (as cholecalciferol) | 400 IU | 100%
Vitamin E (as dl-alpha-tocopheryl acetate) | 40 IU | 133%
Thiamin (Vitamin B1 as thiamin HCl) | 4 mg | 267%
Riboflavin (Vitamin B2) | 4 mg | 235%
Niacin (as niacinamide) | 20 mg | 100%
Vitamin B6 (as pyridoxine HCl) | 20 mg | 1000%
Folate (as folic acid) | 1250 mcg | 313%
Vitamin B12 (as cyanocobalamin) | 30 mcg | 500%
Iron (as carbonyl iron) | 75 mg | 417%
Magnesium (as magnesium oxide) | 30 mg | 8%
Zinc (as zinc oxide) | 20 mg | 133%
Copper (as cupric oxide) | 1 mg | 50%

OTHER INGREDIENTS

Coating (FD&C Blue#2 Lake, FD&C Red#40 Lake, FD&C Yellow#6 Lake, hydroxypropyl methylcellulose, polyvinyl alcohol, talc, titanium dioxide, triacetin), croscarmellose sodium, magnesium stearate, microcrystalline cellulose, pregelatinized starch, silica, silicon dioxide, and stearic acid.

CLINICAL PHARMACOLOGY

Iron is an essential component in the formation of hemoglobin. Adequate amounts of iron are necessary for effective erythropoiesis. Iron also serves as a cofactor of several essential enzymes, including cytochromes that are involved in electron transport. Folic acid is required for nucleoprotein synthesis and the maintenance of normal erythropoiesis. Folic acid is converted in the liver and plasma to its metabolically active form, tetrahydrofolic acid, by dihydrofolate reductase. Vitamin B12 is required for the maintenance of normal erythropoiesis, nucleoprotein and myelin synthesis, cell reproduction and normal growth. Intrinsic factor, a glycoprotein secreted by the gastric mucosa, is required for active absorption of vitamin B12 from the gastrointestinal tract.

INDICATIONS AND USAGE

ACTIVE FE™ is an oral prescription multi-vitamin/multi-mineral dietary supplement for the use in improving the nutritional status of patients with iron deficiency. [This statement has not been evaluated by the FDA. This product is not intended to diagnose, treat, cure, or prevent disease.]

CONTRAINDICATIONS

ACTIVE FE™ is contraindicated in patients with a known hypersensitivity to any of the components of this product. Hemolytic anemia, hemochromatosis and hemosiderosis are contraindications to iron therapy.

WARNINGS

Folic acid alone is improper therapy in the treatment of pernicious anemia and other megaloblastic anemias where vitamin B12 is deficient.

WARNING Accidental overdose of iron-containing products is a leading cause of fatal poisoning in children under 6. KEEP THIS PRODUCT OUT OF THE REACH OF CHILDREN. In case of accidental overdose, call a doctor or poison control center immediately.

Call your doctor about side effects. You may report side effects by calling Allegis Pharmaceuticals, LLC at 1-866-633-9033.

PRECAUTIONS

General

Do not exceed recommended dose. The type of anemia and the underlying cause or causes should be determined before starting therapy with ACTIVE FE™. Since the anemia may be a result of a systemic disturbance, such as recurrent blood loss, the underlying cause or causes should be corrected, if possible.

Folic Acid

Folic acid in doses above 0.1 mg daily may obscure pernicious anemia in that hematologic remission can occur while neurological manifestations remain progressive. Pernicious anemia should be excluded before using this product since folic acid may mask the symptoms of pernicious anemia.

Pediatric Use

Safety and effectiveness in pediatric patients have not been established.

Geriatric Use

Clinical studies on this product have not been performed in subjects aged 65 and over to determine whether elderly subjects respond differently from younger subjects. In general, dose selection for an elderly patient should be cautious and start at the lower end of the dosing range.

ADVERSE REACTIONS

Adverse reactions with iron therapy may include GI irritations, constipation, diarrhea, nausea, vomiting, dark stools and abdominal pain. Adverse reactions with iron therapy are usually transient. Allergic sensitization has been reported following both oral and parenteral administration of folic acid.

Carbonyl iron based products may decrease the absorption of medicines. Talk to your doctor and pharmacist before taking carbonyl products if you take any prescription or over-the-counter medicines.

OVERDOSAGE

The clinical course of acute iron overdosage can be variable. Initial symptoms may include abdominal pain, nausea, vomiting, diarrhea, tarry stools melena, hematemesis, hypotension, tachycardia, metabolic acidosis, hyperglycemia, dehydration, drowsiness, pallor, cyanosis, lassitude, seizures, shock and coma.

DIRECTIONS

Adults

Take one tablet daily, or as prescribed by a licensed medical practitioner.

Children under 12

Consult a doctor.

Pregnant or Nursing

Consult a doctor.

HEALTH CLAIM

DO NOT EXCEED THE RECOMMENDED DOSE.

HOW SUPPLIED

ACTIVE FE™ is supplied as red capsule shaped tablets with imprint FE1 in child-resistant bottles containing 30 tablets. (28595-433-30 [This product is a prescription-folate with or without other dietary ingredients that – due to increased folate levels (AUG 2 1973 FR 20750), requires an Rx on the label because of increased risk associated with masking of B12 deficiency (pernicious anemia). Based on our assessment of the risk of obscuring pernicious anemia, this product requires licensed medical supervision, an Rx status, and a National Drug Code (NDC) – or similarly-formatted product code, as required by pedigree reporting requirements and supply-chain control as well as – in some cases, for insurance-reimbursement applications.All prescriptions using this product shall be pursuant to state statutes as applicable. This is not an Orange Book product. This product may be administered only under a physician's supervision. There are no implied or explicit claims on therapeutic equivalence.])

STORAGE

Store at 20°-25°C (68°-77°F); excursions permitted to 15°-30°C (59°-86°F). [See USP Controlled Room Temperature.] Protect from light and moisture. Dispense in a tight, light-resistant container.

KEEP OUT OF REACH OF CHILDREN.

HEALTH CLAIM

Rx
MADE IN CANADA

MANUFACTURED FOR:
Allegis Pharmaceuticals, LLC
Canton, MS 39046

Rev. 01/2016
Covered by U.S. Patent# 7998500

PRINCIPAL DISPLAY PANEL - 30 Tablet Bottle Label

28595-433-30

ACTiVE FE™

Iron Supplement

ALLEGIS PHARMACEUTICALS

30 Tablets
Rx

Manufactured for:
Allegis Pharmaceuticals, LLC
Canton, MS 39046

Lactose, Gluten and Sugar Free